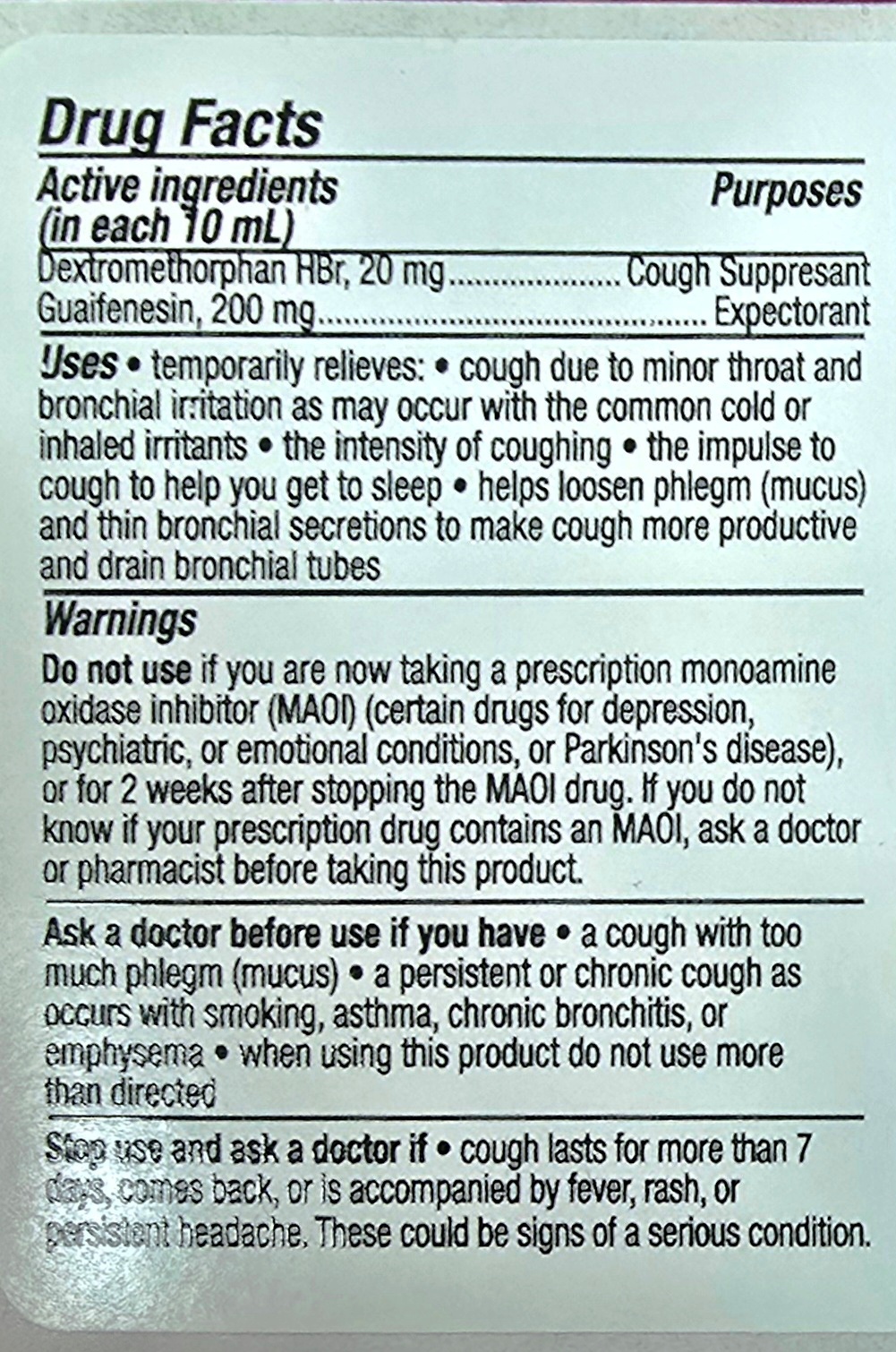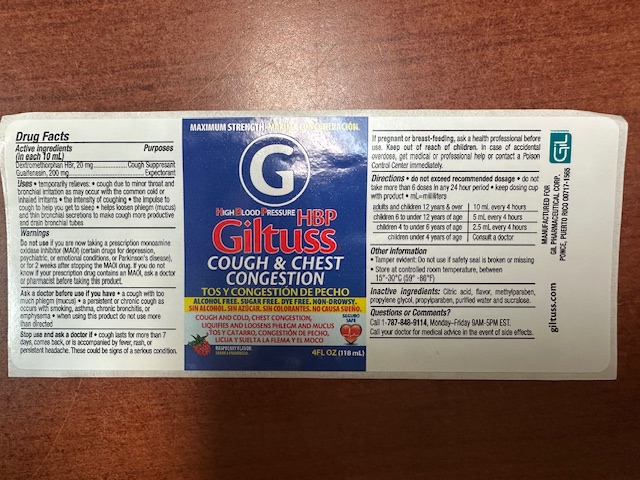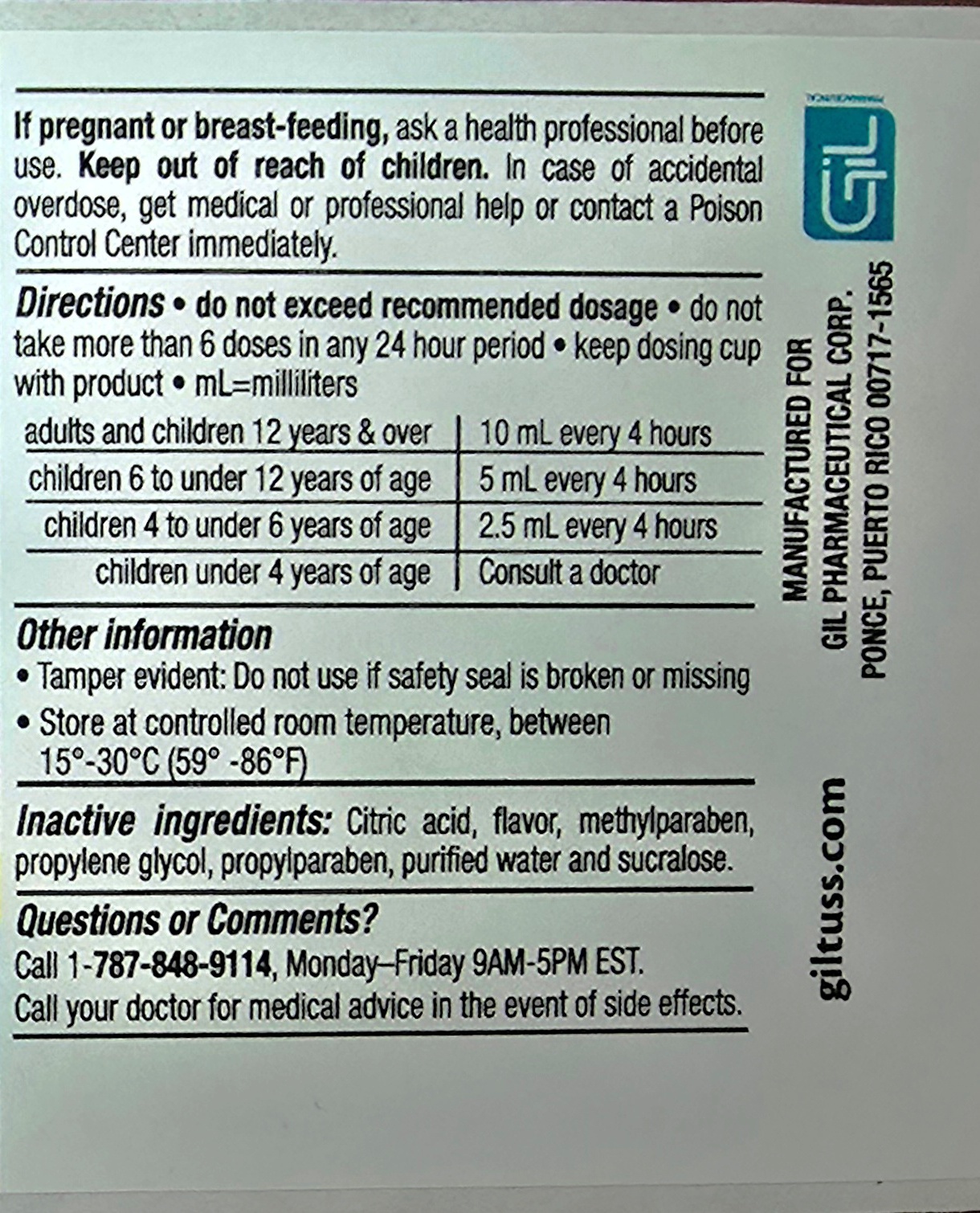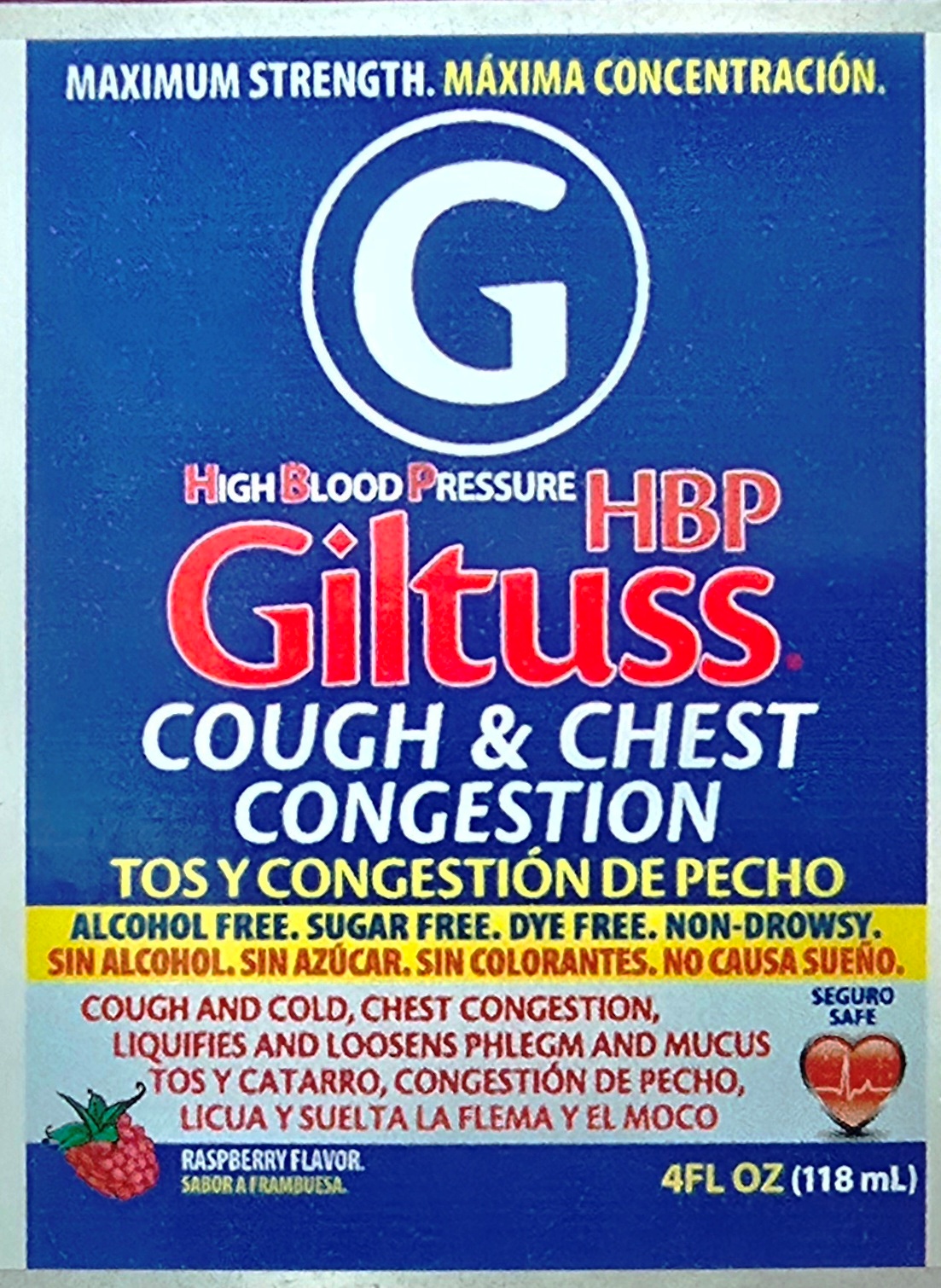 DRUG LABEL: Giltuss HBP Cough and Chest Congestion
NDC: 65852-006 | Form: SOLUTION
Manufacturer: Dextrum Laboratories Inc.
Category: otc | Type: HUMAN OTC DRUG LABEL
Date: 20250922

ACTIVE INGREDIENTS: GUAIFENESIN 200 mg/10 mL; DEXTROMETHORPHAN HYDROBROMIDE 20 mg/10 mL
INACTIVE INGREDIENTS: CITRIC ACID; RASPBERRY; PROPYLPARABEN; METHYLPARABEN; WATER; SUCRALOSE; PROPYLENE GLYCOL

Giltuss HBP Cough and Chest Congestion

Active ingredients

Dextromethorphan HBr, 20 mg

Guaifenesin, 200 mg

Purposes and Uses

Purposes

Cough supresant

Expectorant

Uses

Temporary relieves, cough due to minor throat and bronchial irritation as may occur with the common cold or inhaled irritants , the intensity of coughing, the impulse to cough to help you get to sleep, help loosen phlegm (mucus) and thin bronchial secretions to make cough more productive and drain bronchial tubes

Warnings

Do not use

If you are taking a prescription monoamine oxidase inhibitor (MAOI) (certains drugs for depression, psychiatric, or emotional conditions, or Parkinson's disease), or for 2 weeks after stopping the MAOI drug. If you dont know is your prescription drug contains and MAOI, ask a doctor or pharmacist before taking this product.

Ask a doctor before use if you have, a cough with too much phlegm(mucus) , a persistent or chronic cough as occurs with smoking, asthma, chronic bronchitis, or emphysema, when using this product do not use more than directed.

Stop use and ask a doctor if

cough lasts for more than 7 days , come back, or is accompanied by fever, rash or persistent headache. These could be signs of serious condition.

If pregnant

If pregnant or breast- feeding, ask a health professional before use. Keep out of reach of children. In case of accidental overdose, get medical or professional help or contact a Poisson Control center immediately

Directions

Do not exceed recommended dosage

Do not take more than 6 doses in any 24 hours period

Keep dosing cup with product

ml= mililiters

Adults and children 12 years & over 10 ml every 4 hours

children 6 to under 12 years of age 5 ml every 4 hours

children 4 to under 6 years of age 2.5 ml every 4 hours

children under 4 years of age Consult a doctor

Other information

Tamper evident : Do not use if safety seal is broken or missing

Store at controlled room temperature 15-30 °C (59° -86 ° F)

Inactive Ingredients

Citric Acid, flavor, methylparaben, propylene glycol, propylparaben, purified water and sucralose

Questions or comments

Call 1-787-848-9114, Monday-Friday 9AM – 5PM EST

Call your doctor for medical advice in the event of side effects.

keep out of seach children

keep out of reach of the children.

In case of accidental overdose get medical professional helph or contact a Poison Control Center immediately

Indication and usage

Do not exceed recommended dosage

Do not take more than 6 doses in any 24 hours period

Keep dosing cup with product

ml= mililiters

Adults and children 12 years & over 10 ml every 4 hours

children 6 to under 12 years of age 5 ml every 4 hours

children 4 to under 6 years of age 2.5 ml every 4 hours

children under 4 years of age Consult a doctor

Principal panel

Maximum strength

High Blood Pressure

Giltuss HBP

Cough & Chest Congestion

Alcohol free, Sugar Free, Dye free, Non -Drowsy

Cough and cold, chest congestion, liquifies and loosens phlegm and mucus

Raspberry flavor

4 floz 118 ml